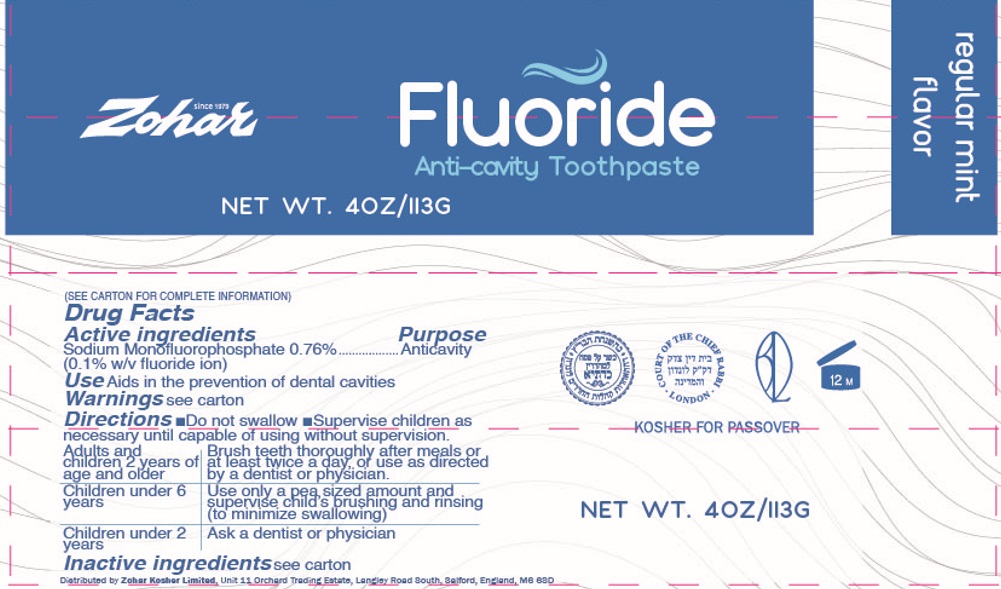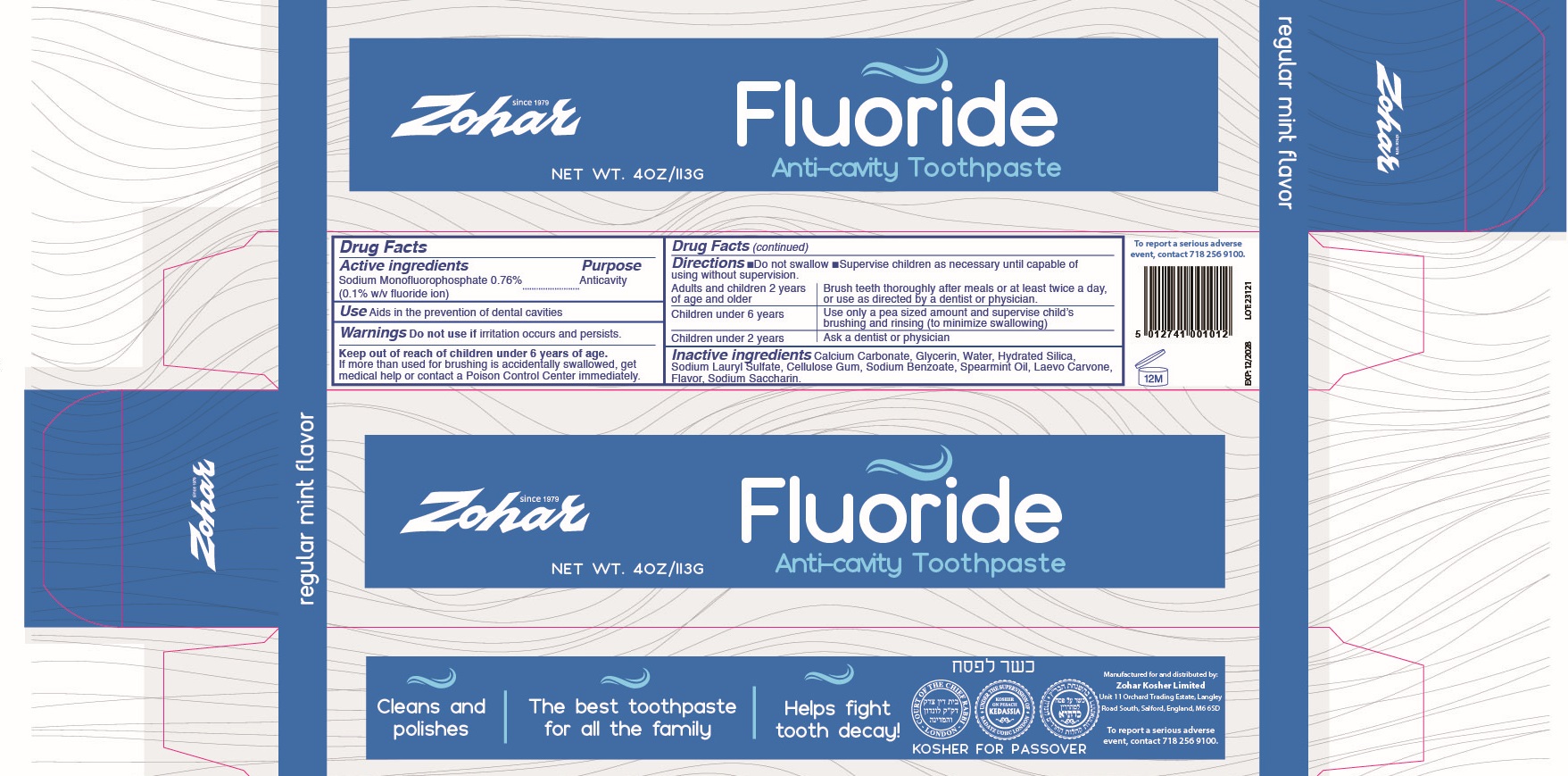 DRUG LABEL: Zohar Fluoride Anti-Cavity Regular Mint Flavour
NDC: 84045-005 | Form: PASTE
Manufacturer: ZOHAR KOSHER LIMITED
Category: otc | Type: HUMAN OTC DRUG LABEL
Date: 20240227

ACTIVE INGREDIENTS: SODIUM MONOFLUOROPHOSPHATE 7.6 mg/1 g
INACTIVE INGREDIENTS: CALCIUM CARBONATE; GLYCERIN; WATER; HYDRATED SILICA; SODIUM LAURYL SULFATE; CARBOXYMETHYLCELLULOSE SODIUM, UNSPECIFIED; SODIUM BENZOATE; SPEARMINT OIL; SACCHARIN SODIUM

Zohar Fluoride Anti-Cavity Toothpaste Regular Mint Flavour

Active ingredients

Sodium Monofluorophosphate 0.76% (0.1% w/v fluoride ion)

Purpose

Anticavity

Use

Aids in the prevention of dental cavities

Warnings

Do not use if

irritation occurs and persists.

Keep out of reach of children under 6 years of age.

If more than used for brushing is accidentally swallowed, get medical help or contact a Poison Control Center immediately.

Directions

• Do not swallow • Supervise children as necessary until capable of using without supervision.

Adults and children 2 years of age and older | Brush teeth thoroughly after meals or at least twice a day, or use as directed by a dentist or physician.
Children under 6 years | Use only a pea sized amount and supervise child's brushing and rinsing (to minimize swallowing)
Children under 2 years | Ask a dentist or physician

Inactive ingredients

Calcium Carbonate, Glycerin, Water, Hydrated Silica, Sodium Lauryl Sulfate, Cellulose Gum, Sodium Benzoate, Spearmint Oil, Laevo Carvone, Flavor, Sodium Saccharin.